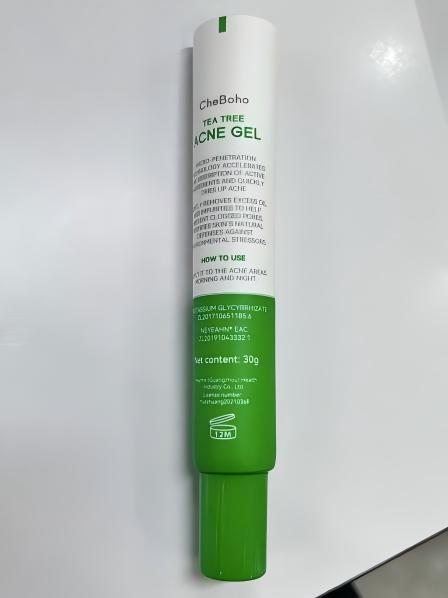 DRUG LABEL: CheBoho TEA TREE ACNE
NDC: 87136-362 | Form: GEL
Manufacturer: Opalshi(Guangzhou)E-commerce Co. Ltd.
Category: homeopathic | Type: HUMAN OTC DRUG LABEL
Date: 20250927

ACTIVE INGREDIENTS: BUTYLENE GLYCOL 9 g/1 1; WATER 84 g/1 1
INACTIVE INGREDIENTS: SODIUM ACETYLATED HYALURONATE; MADECASSOSIDE; PROPANEDIOL; POTASSIUM SORBATE; GLYCERIN; CITRIC ACID; MALTODEXTRIN; ASIATICOSIDE; BENZYL GLYCOL; PEG-9 DIGLYCIDYL ETHER/SODIUM HYALURONATE CROSSPOLYMER; ALUMINUM DICHLOROHYDREX PROPYLENE GLYCOL; 1,2-HEXANEDIOL; PEG-60 HYDROGENATED CASTOR OIL; NIACINAMIDE; MELALEUCA ALTERNIFOLIA (TEA TREE) LEAF OIL; XANTHAN GUM; O-CYMEN-5-OL; QUATERNIUM-73; ALOE BARBADENSIS LEAF JUICE; SODIUM HYALURONATE; HAMAMELIS VIRGINIANA (WITCH HAZEL) LEAF WATER; MENTHONE GLYCERIN ACETAL; CAMELLIA JAPONICA SEED OIL; PEG-40 HYDROGENATED CASTOR OIL; PANTHENOL; HOUTTUYNIA CORDATA WHOLE; DIPOTASSIUM AZELATE; PHENOXYETHANOL; HYDROLYZED GLYCOSAMINOGLYCANS (BOVINE; 50000 MW); MENTHYL LACTATE; CARBOMER; 3',5'-DIBROMO-4'-HYDROXYACETOPHENONE; ETHYLHEXYLGLYCERIN; PENTYLENE GLYCOL; ARGININE; ALLANTOIN; CAPRYLYL GLYCOL; PPG-26-BUTETH-26; HYALURONIC ACID

Keep out of reach of children

ACTIVE INGREDIENT

WATER,UTYLENE GLYCOL

Keep out of reach of children section

PURPOSE

Prevent and reduce the occurrence of acne, relieve inflammation and redness.

DOSAGE AND ADMINISTRATION

Take a small amount and apply it to the skin.

INDICATIONS AND USAGE

Take a small amount and apply it to the skin.Relieve inflammation and swelling

INACTIVE INGREDIENT

GLYCERIN,CARBOMER,ARGININE,PROPYLENE GLYCOL,1,2-HEXANEDIOL,HYDROXYACETOPHENONE,PEG-40 HYDROGENATED CASTOR OIL,PEG-60 HYDROGENATED CASTOR OIL,PPG-26-BUTETH-26